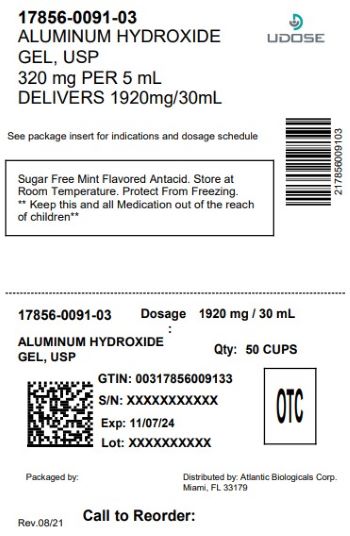 DRUG LABEL: Aluminum Hydroxide

NDC: 17856-0091 | Form: LIQUID
Manufacturer: ATLANTIC BIOLOGICALS CORP.
Category: otc | Type: HUMAN OTC DRUG LABEL
Date: 20251215

ACTIVE INGREDIENTS: ALUMINUM HYDROXIDE 320 mg/5 mL
INACTIVE INGREDIENTS: BENZYL ALCOHOL; BUTYLPARABEN; GLYCERIN; HYDROXYETHYL CELLULOSE (4000 MPA.S AT 1%); DIMETHICONE; PROPYLPARABEN; WATER; SACCHARIN SODIUM; SORBITOL

Active ingredient (in each 5 mL teaspoonful)

Aluminum hydroxide 320 mg

Purpose

Antacid

Uses

relieves

- heartburn
- acid indigestion
- sour stomach

Warnings

taking a prescription drug. Antacids may interact with certain prescription drugs. you may get constipated symptoms last more than 2 weeks

Ask a doctor or pharmacist before use if you are

When using this product

Stop use and ask a doctor if

Keep out of reach of children.

Directions

• shake well before using • do not take more than 12 teaspoonfuls in 24 hours • do not use the maximum dosage for more than 2 weeks • 2 teaspoonfuls 5-6 times daily after meals and at bedtime followed by a sip of water if needed

dosage:

Other information

• store at room temperature • protect from freezing • keep tightly closed •
TAMPER-EVIDENT: DO NOT USE IF FOIL SEAL UNDER CAP IS BROKEN OR MISSING.

Inactive ingredients

benzyl alcohol, butylparaben, flavor, glycerin, hydroxyethylcellulose, propylparaben, purified water, saccharin sodium, simethicone emulsion, sorbitol solution

Questions or comments?

Call 9am - 5pm EST, Monday-Friday 1-800-509-7592

DISTRIBUTED BY:

ATLANTIC BIOLOGICALS CORP.

MIAMI, FL 33179